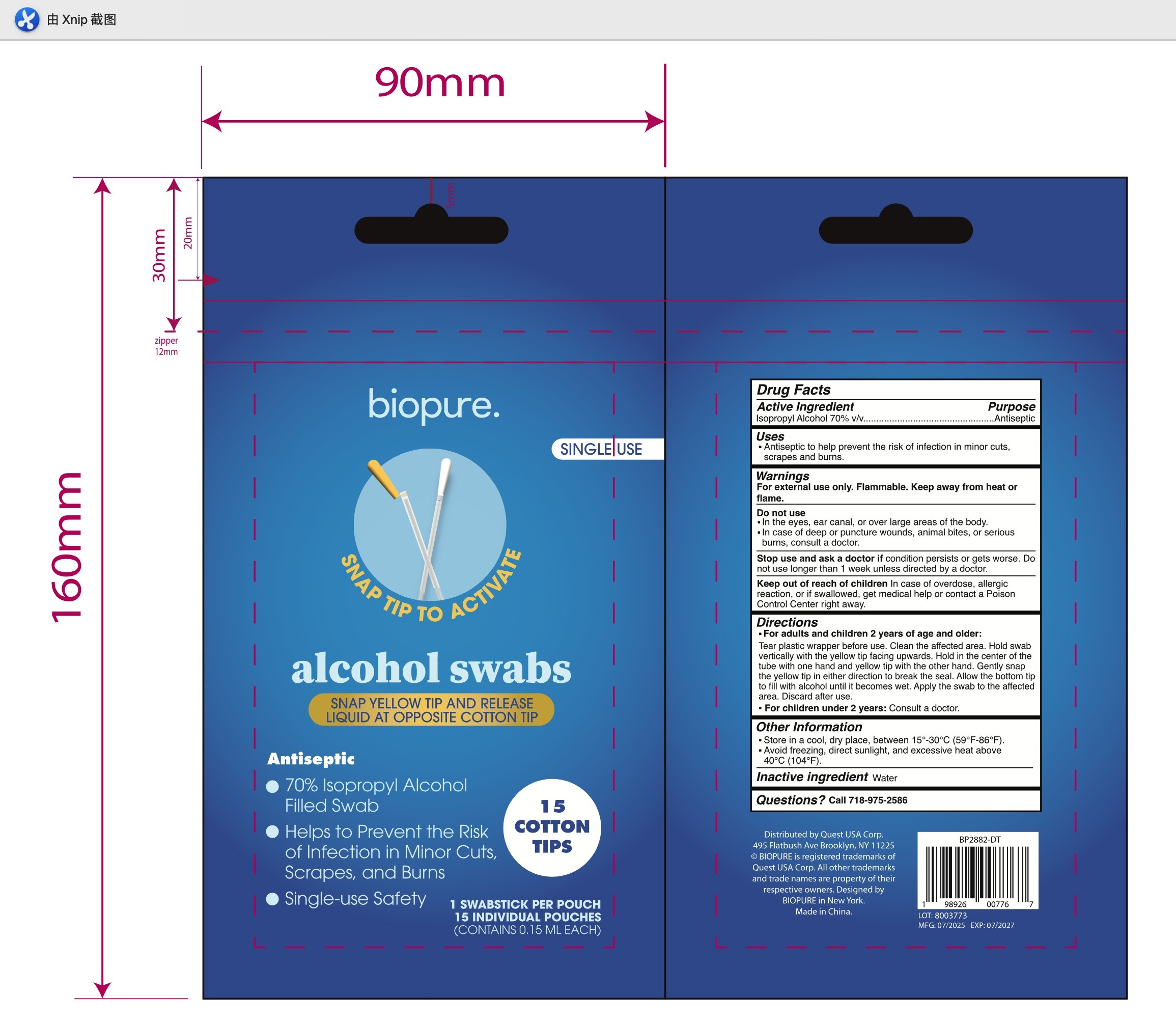 DRUG LABEL: Biopure Alcohol Cotton Swabs
NDC: 78691-031 | Form: SWAB
Manufacturer: QUEST USA CORP
Category: otc | Type: HUMAN OTC DRUG LABEL
Date: 20250719

ACTIVE INGREDIENTS: ISOPROPYL ALCOHOL 0.15 mL/1 mL
INACTIVE INGREDIENTS: WATER

BIOPURE Alcohol Cotton Swab

Active ingredient

Isopropyl Alcohol 70% v/v

Purpose

Antiseptic

Uses

Antiseptic to help prevent the risk of infection in minor cuts, scrapes, and burns.

Warnings

For external use only. Flammable. Keep away from heat or flame.

Stop use and ask a doctor

if the condition persists or gets worse. Do not use longer than 1 week unless directed by a doctor.

Do not use

- in the eyes, ear canal, or apply over large areas of the body.
- In case of deep or puncture wounds, animal bites, or serious burns, consult a doctor.

Keep out of reach of children. In case of overdose, allergic reaction, or if swallowed, get medical help or contact a Poison Control Center right away.

Directions

- For adults and children 2 years of age and older: Tear plastic wrapper before use. Clean the affected area. Hold swab vertically with the yellow tip facing upwards. Hold in the center of the tube with one hand and yellow tip with the other hand. Gently snap the yellow tip in either direction to break the seal. Allow the bottom tip to fill with alcohol until it becomes wet. Apply the swab to the affected area. Discard after use.
- For children under 2 years: Consult a doctor.

Other information

- Store in a cool, dry place, between 15°-30°C(59°F-86°F).
- Avoid freezing, direct sunlight, and excessive heat above 40°C(104°F).

Inactive ingredients

Water

Questions?

Call 718-975-2586